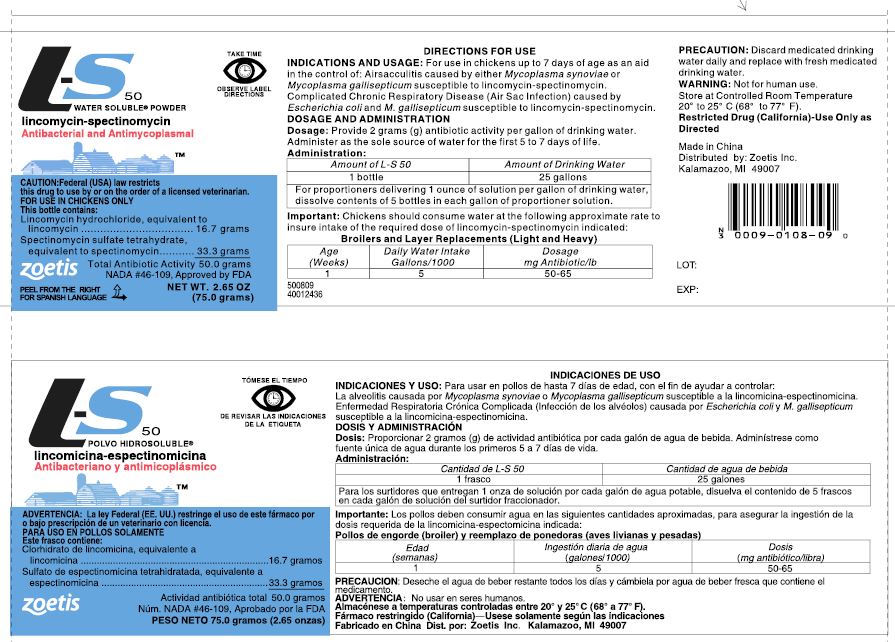 DRUG LABEL: L-S 50
NDC: 54771-1108 | Form: POWDER, FOR SOLUTION
Manufacturer: Zoetis Inc.
Category: animal | Type: PRESCRIPTION ANIMAL DRUG LABEL
Date: 20231201

ACTIVE INGREDIENTS: LINCOMYCIN HYDROCHLORIDE 16.7 g/75 g; SPECTINOMYCIN SULFATE TETRAHYDRATE 33.3 g/75 g

L-S 50
WATER SOLUBLE® POWDER
lincomycin-spectinomycin

L-S 50
WATER SOLUBLE® POWDER
lincomycin-spectinomycin
Antibacterial and Antimycoplasmal
CAUTION: Federal law restricts this drug to use by or on the order of a licensed veterinarian.
FOR USE IN CHICKENS ONLY

INDICATIONS AND USAGE

For use in chickens up to 7 days of age as an aid in the control of: Airsacculitis caused by either Mycoplasma synoviae or Mycoplasma gallisepticum susceptible to lincomycin-spectinomycin. Complicated Chronic Respiratory Disease (Air Sac Infection) caused by Escherichia coli and M. gallisepticum susceptible to lincomycin-spectinomycin.

Complicated Chronic Respiratory Disease (Air Sac Infection) caused by Escherichia coli and M. gallisepticum susceptible to lincomycin-spectinomycin.

DOSAGE AND ADMINISTRATION

Dosage

Provide 2 grams (g) antibiotic activity per gallon of drinking water. Administer as the sole source of water for the first 5 to 7 days of life.

Administration

Amount of L-S 50 | Amount of Drinking Water
1 bottle | 25 gallons
For proportioners delivering 1 ounce of solution per gallon of drinking water, dissolve contents of 5 bottles in each gallon of proportioner solution.

INFORMATION FOR OWNERS/CAREGIVERS

Important: Chickens should consume water at the following approximate rate to insure intake of the required dose of lincomycin-spectinomycin indicated:

Broilers and Layer Replacements (Light and Heavy)
Age (Weeks) | Daily Water Intake Gallons/1000 | Dosage mg Antibiotic/lb
1 | 5 | 50-65

PRECAUTION

Discard medicated drinking water daily and replace with fresh medicated drinking water.

WARNING

Not for human use.

Storage

Store at Controlled Room Temperature 20° to 25° C (68° to 77° F).

SAFE HANDLING WARNING

Restricted Drug (California)-Use Only as Directed

Made in China
Distributed by: Zoetis Inc.
Kalamazoo, MI 49007

500809
40039820

PRINCIPAL DISPLAY PANEL - 75 g Bottle Label

TAKE TIME
OBSERVE LABEL
DIRECTIONS

This bottle contains:

Lincomycin hydrochloride, equivalent to
lincomycin
16.7 grams

Spectinomycin sulfate tetrahydrate,
equivalent to spectinomycin
33.3 grams

Total Antibiotic Activity
50.0 grams

zoetis

Approved by FDA under NADA # 046-109

PEEL FROM THE RIGHT
FOR SPANISH LANGUAGE

NET WT. 2.65 OZ
(75.0 grams)